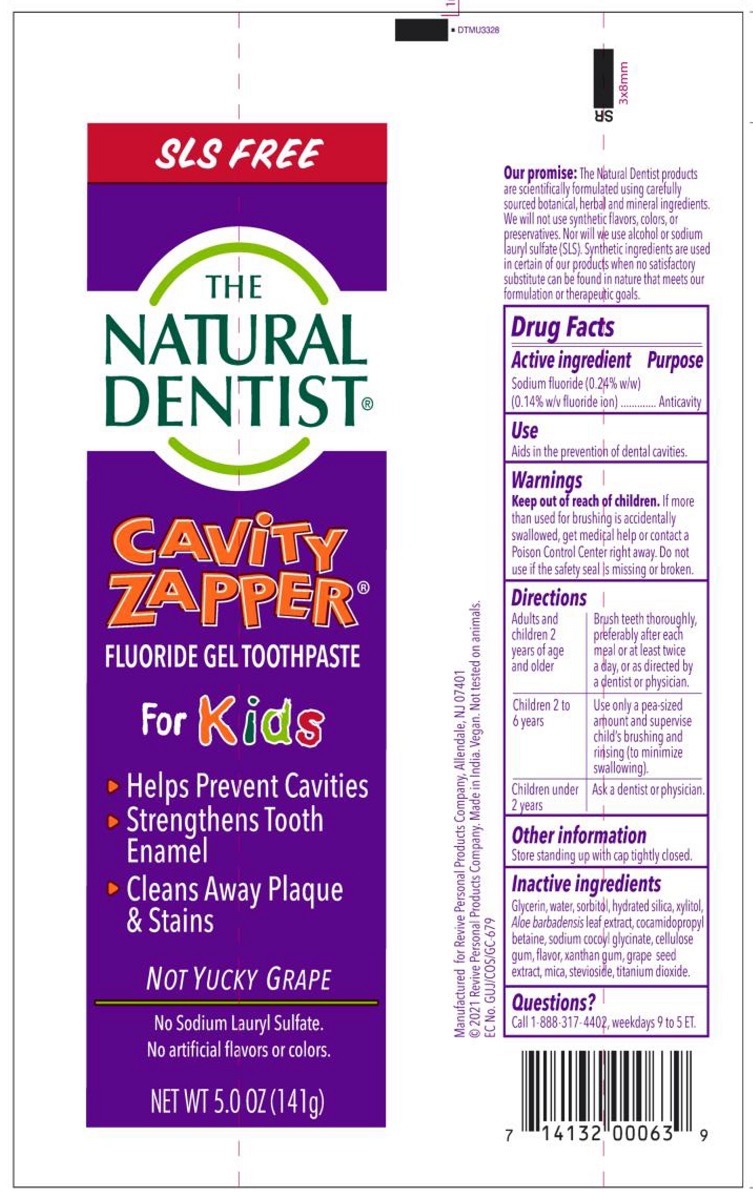 DRUG LABEL: The Natural Dentist
NDC: 34362-0233 | Form: PASTE, DENTIFRICE
Manufacturer: Caldwell Consumer Health LLC
Category: otc | Type: HUMAN OTC DRUG LABEL
Date: 20240116

ACTIVE INGREDIENTS: SODIUM FLUORIDE 0.243 g/100 g
INACTIVE INGREDIENTS: WATER; SORBITOL; XYLITOL; STEVIA REBAUDIUNA LEAF; ALOE VERA LEAF; TITANIUM DIOXIDE; GLYCERIN; CARBOXYMETHYLCELLULOSE SODIUM, UNSPECIFIED FORM; HYDRATED SILICA; XANTHAN GUM; GRAPEFRUIT SEED OIL; COCAMIDOPROPYL BETAINE; MICA; SODIUM COCOYL GLYCINATE

The Natural Dentist Cavity Zapper Toothpaste, Grape

Drug Facts

Active ingredient

Sodium fluoride (0.24%)(0.15% w/v fluoride ion)

Purpose

Anticavity

Use

Aids in the prevention of dental cavities.

Warnings

Keep out of reach of children. If more than used for brushing is accidentally swallowed, get medical help or contact a Poison Control Center right away. Do not use if the safety seal is missing or broken.

Directions

Adults and children 2 years of age and older | Brush teeth thoroughly preferably after each meal or at least twice a day, or as directed by a dentist or physician.
Children 2 to 6 years | Use only a pea sized amount and supervise children's brushing and rinsing (to minimize swallowing.)
Children under 2 years | Ask a dentist or physician.

Other information

Store tube standing up with cap tightly closed.

INACTIVE INGREDIENT

Inactive ingredients Glycerin, water, sorbitol, hydrated silica, xylitol, Aloe barbadensis leaf juice, cocamidopropyl betaine, sodium cocoyl glycinate, cellulose gum, flavor, xanthan gum, Citrus grandis (grapefruit) seed extract, mica, Stevia rebaudiana extract, titanium dioxide,

Questions?

Call 1-888-317-4402, weekdays 9 to 5 ET.

Manufactured for Revive Personal Care Products Company Allendale, NJ 07401

©2018 Revive Personal Products Company. Made in the USA. Vegan. Not tested on animals.

PACKAGE LABEL

THE NATURAL DENTIST®

CAVITY ZAPPER®

ANTICAVITY GEL TOOTHPASTE FOR KIDS

- Helps Prevent Cavities
- Strengthens Tooth Enamel
- Cleans Away Plaque & Stains

NOT YUCKY GRAPE

No Sodium Lauryl Sulfate

No artificial flavors or colors.

NET WT 5.0 OZ (141 g)